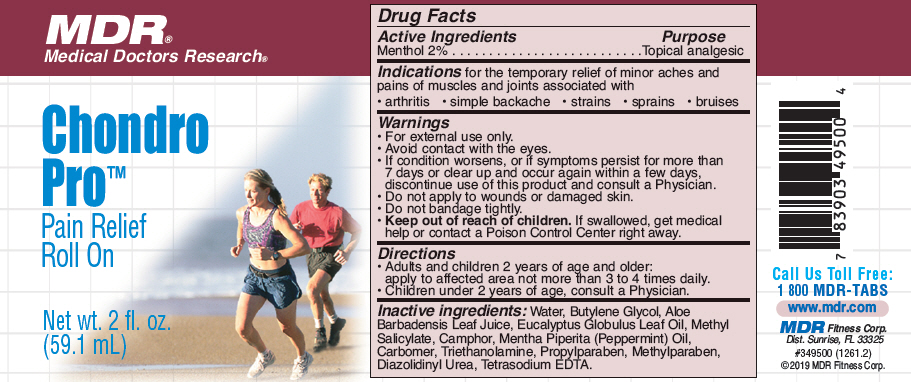 DRUG LABEL: Chondro-Pro 
NDC: 68393-349 | Form: GEL
Manufacturer: MDR Fitness Corp.
Category: otc | Type: HUMAN OTC DRUG LABEL
Date: 20191223

ACTIVE INGREDIENTS: MENTHOL, UNSPECIFIED FORM 1 mg/100 mL
INACTIVE INGREDIENTS: Camphor (synthetic); Water; Eucalyptus oil

Chondro-Pro™
Pain Relief Roll On

Drug Facts

Active Ingredients

Menthol 2%

Purpose

Topical analgesic

Indications

for the temporary relief of minor aches and pains of muscles and joints associated with

- arthritis
- simple backache
- strains
- sprains
- bruises

Warnings

- For external use only.
- Avoid contact with the eyes.
- If condition worsens, or if symptoms persist for more than 7 days or clear up and occur again within a few days, discontinue use of this product and consult a Physician.
- Do not apply to wounds or damaged skin.
- Do not bandage tightly.

- Keep out of reach of children. If swallowed, get medical help or contact a Poison Control Center right away.

Directions

- Adults and children 2 years of age and older:
  apply to affected area not more than 3 to 4 times daily.
- Children under 2 years of age, consult a Physician.

Inactive ingredients

Water, Butylene Glycol, Aloe Barbadensis Leaf Juice, Eucalyptus Globulus Leaf Oil, Methyl Salicylate, Camphor, Mentha Piperita (Peppermint) Oil, Carbomer, Triethanolamine, Propylparaben, Methylparaben, Diazolidinyl Urea, Tetrasodium EDTA.

QUESTIONS

Call Us Toll Free:
1 800 MDR-TABS

PRINCIPAL DISPLAY PANEL - 59.1 mL Bottle Label

MDR®
Medical Doctors Research®

Chondro
Pro™
Pain Relief
Roll On

Net wt. 2 fl. oz.
(59.1 mL)